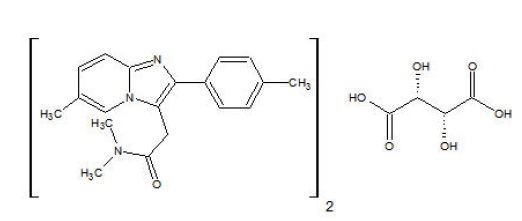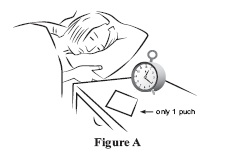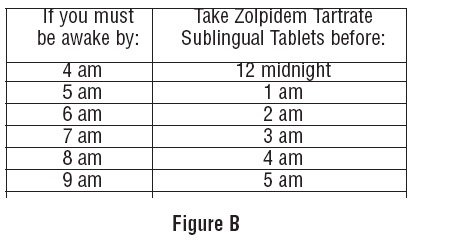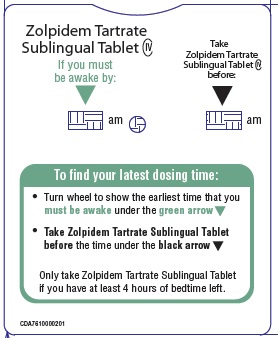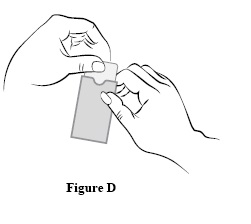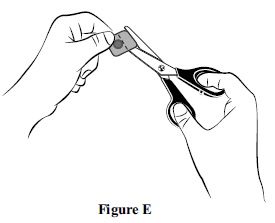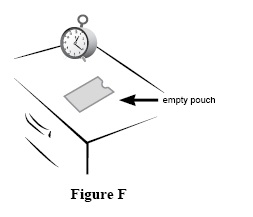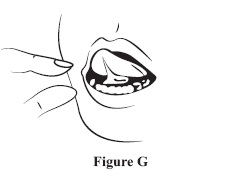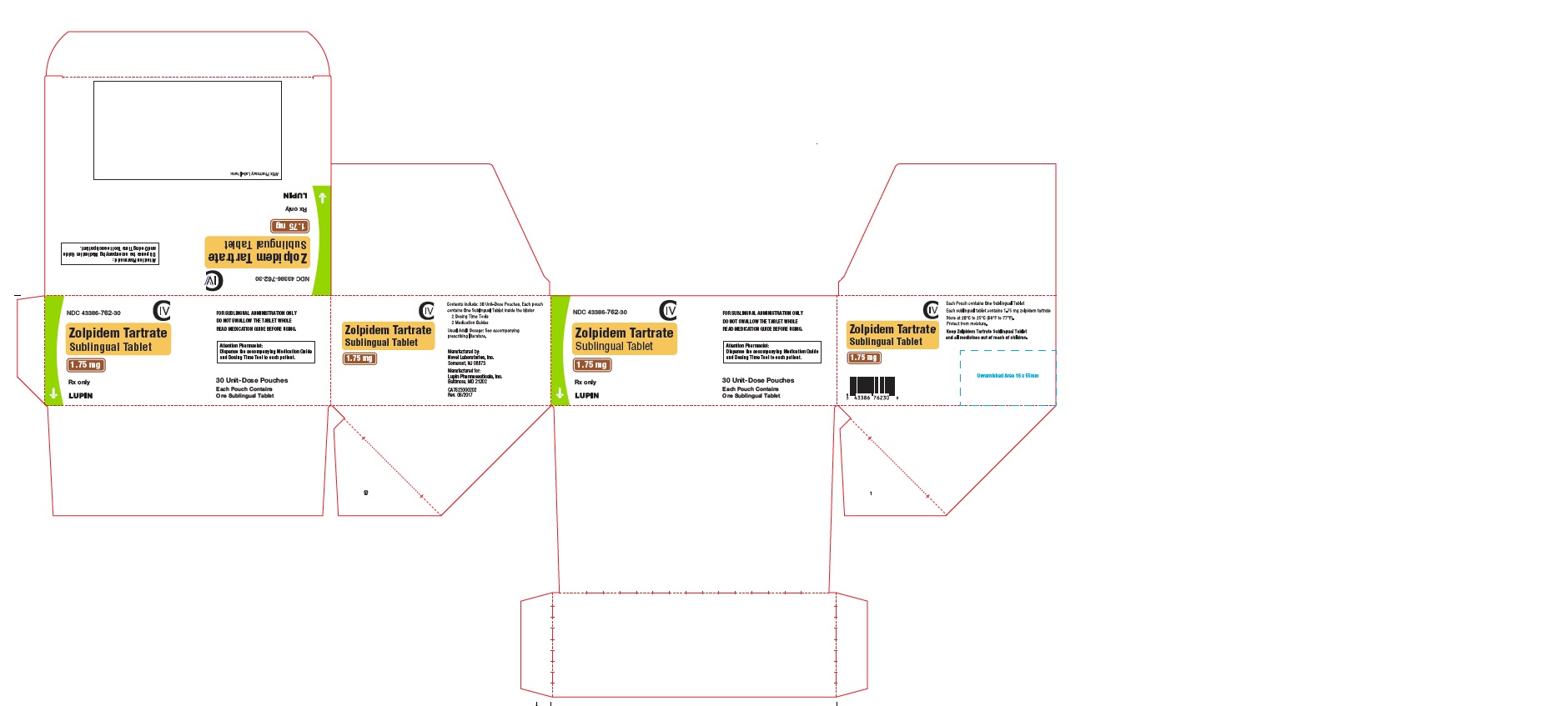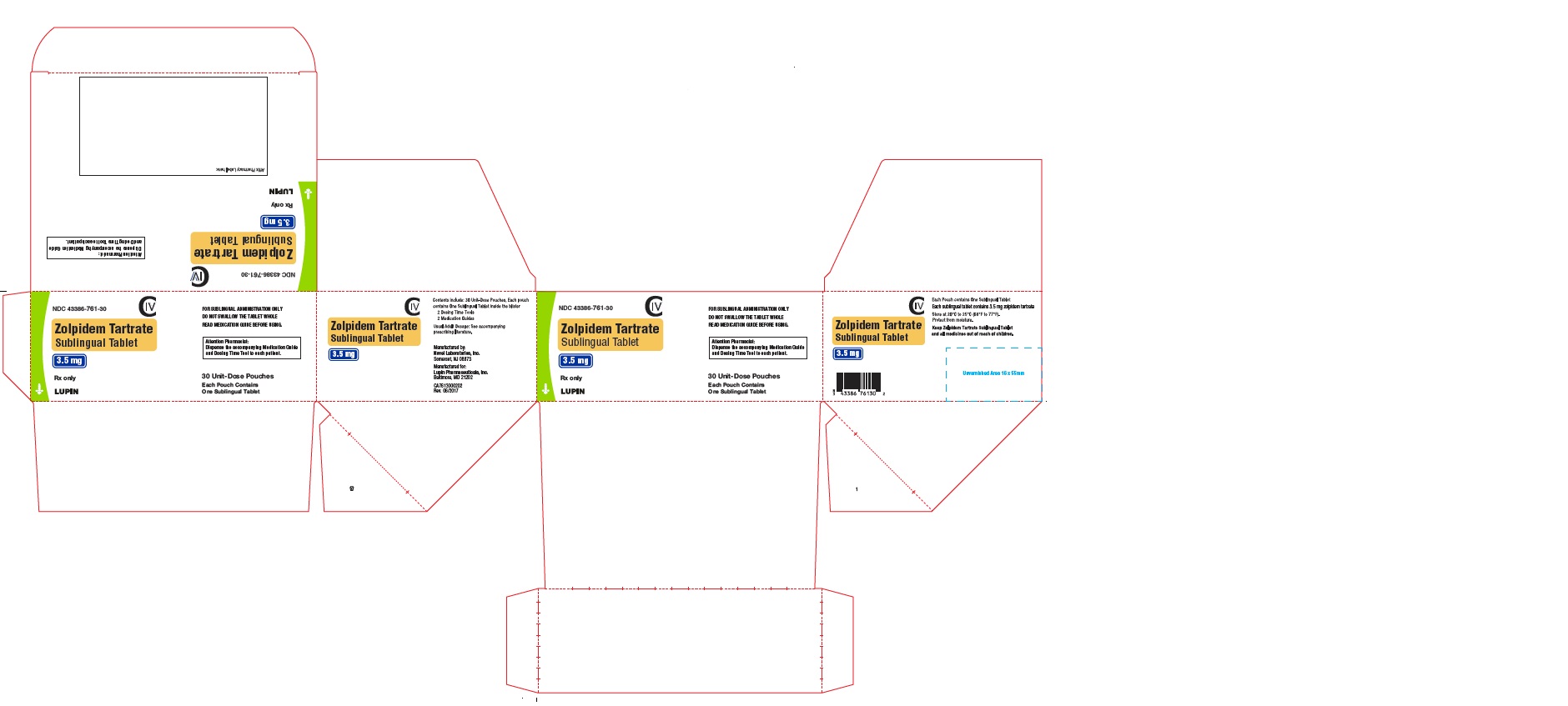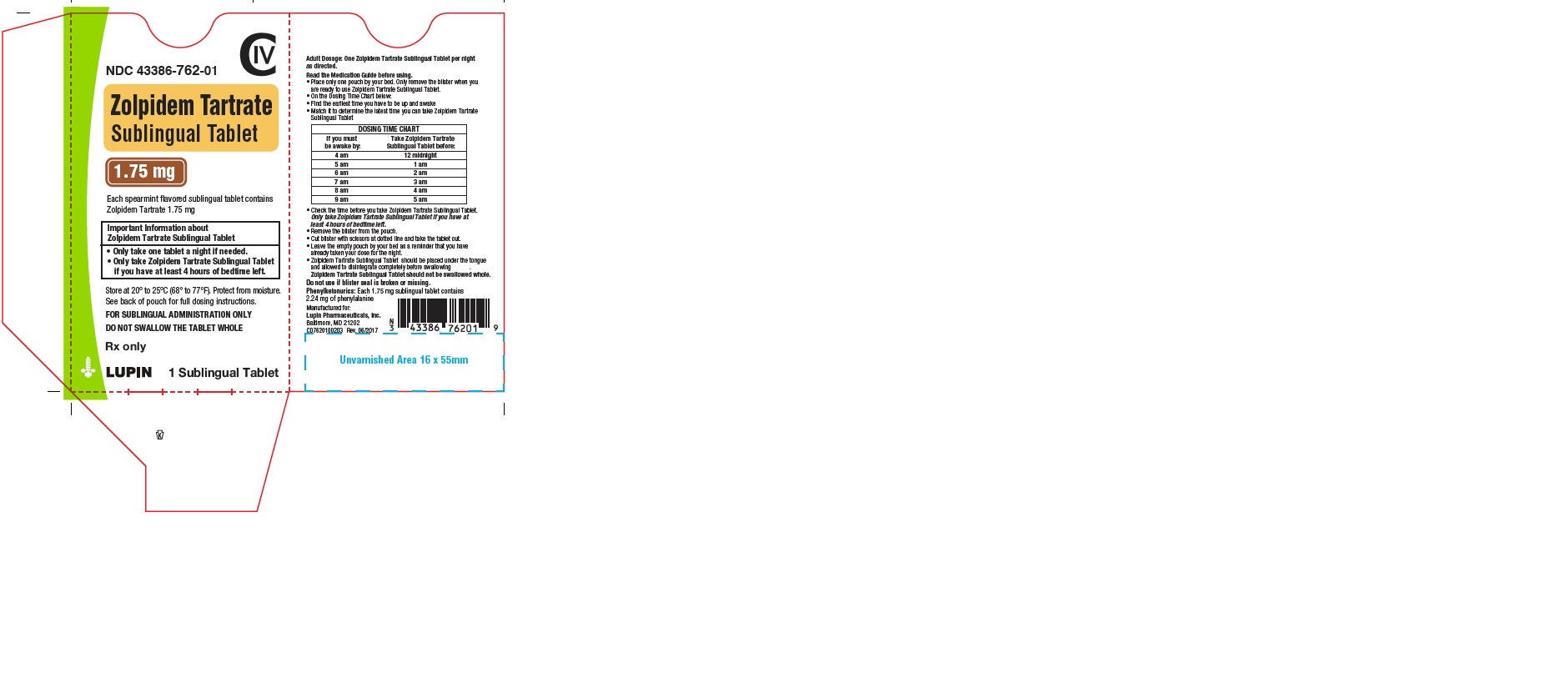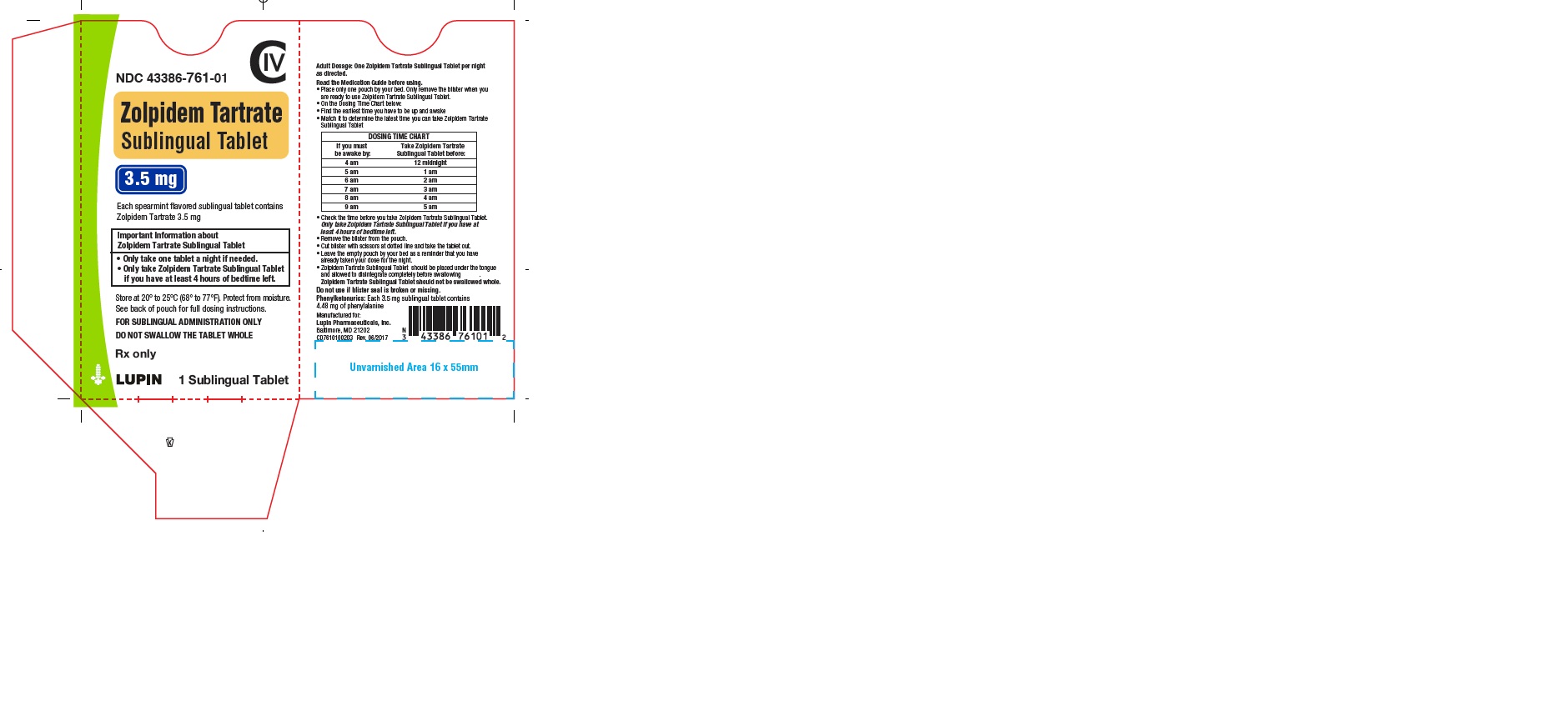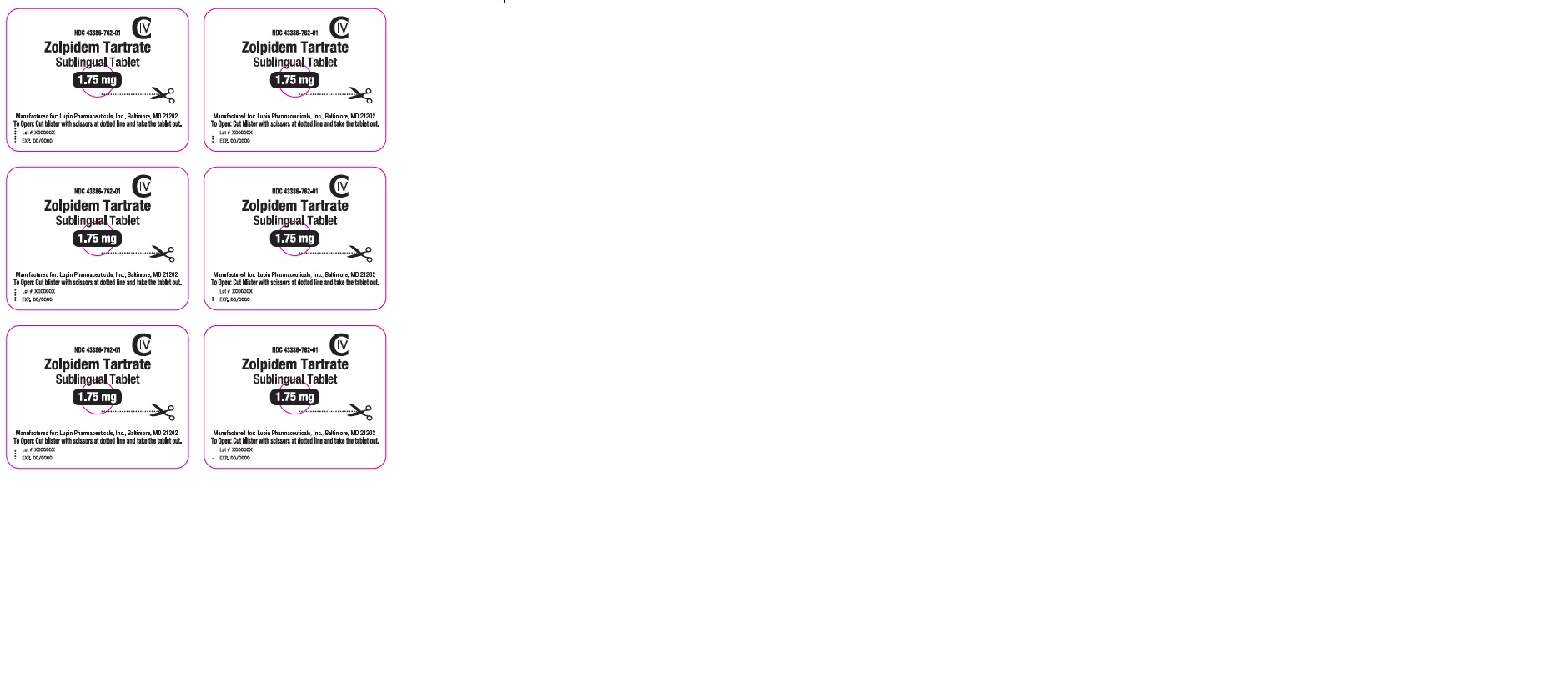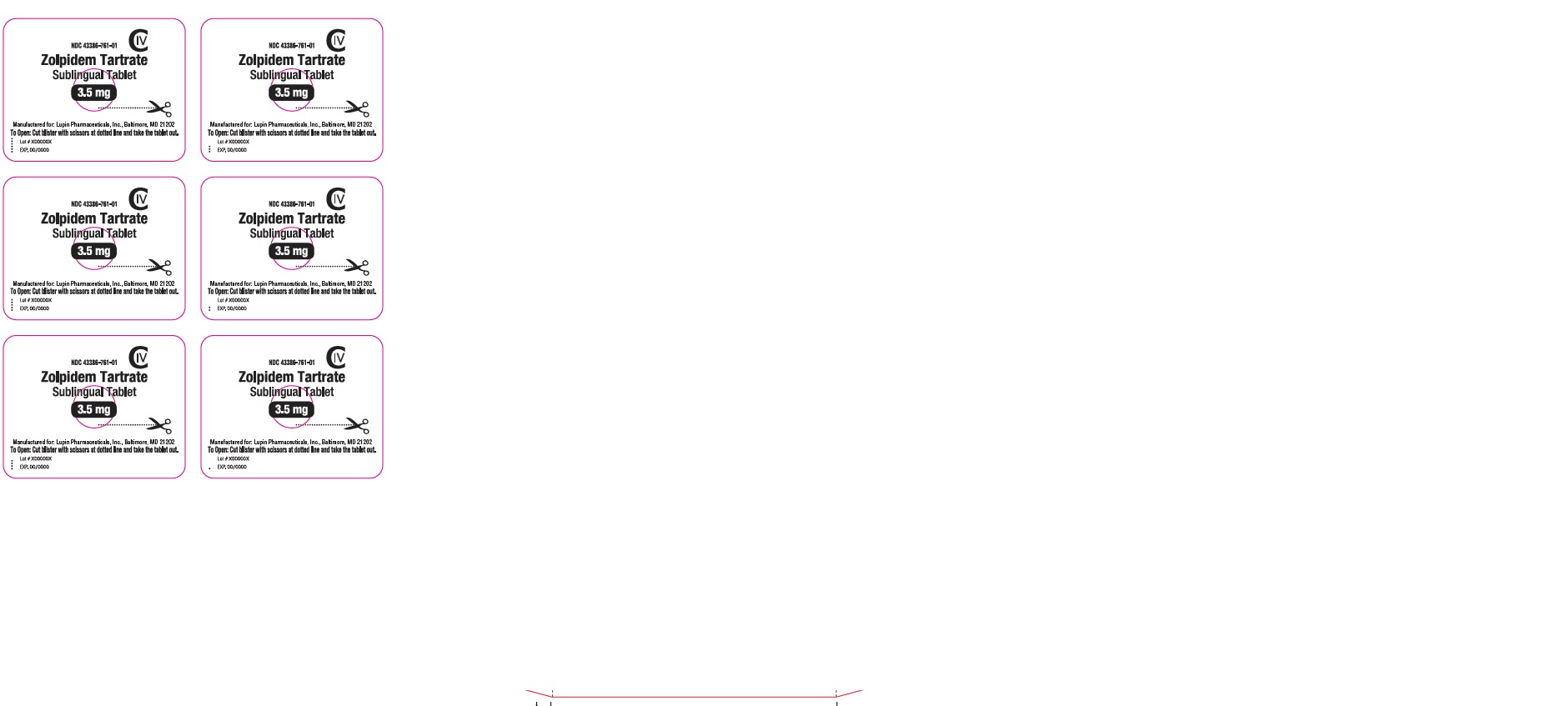 DRUG LABEL: ZOLPIDEM TARTRATE
NDC: 43386-762 | Form: TABLET
Manufacturer: Lupin Pharmaceuticals,Inc.
Category: prescription | Type: HUMAN PRESCRIPTION DRUG LABEL
Date: 20201118
DEA Schedule: CIV

ACTIVE INGREDIENTS: ZOLPIDEM TARTRATE 1.75 mg/1 1
INACTIVE INGREDIENTS: CROSPOVIDONE; POVIDONE; MANNITOL; POLYVINYL ACETATE PHTHALATE; SILICON DIOXIDE; SODIUM CARBONATE; SODIUM BICARBONATE; ASPARTAME; MAGNESIUM STEARATE

HIGHLIGHTS OF PRESCRIBING INFORMATION

These highlights do not include all the information needed to use ZOLPIDEM TARTRATE SUBLINGUAL TABLETS safely and effectively. See full prescribing information for ZOLPIDEM TARTRATE SUBLINGUAL TABLETS.
ZOLPIDEM TARTRATE sublingual tablets, for oral use.
Initial U.S. Approval: 1992

WARNING COMPLEX SLEEP BEHAVIORS

See full prescribing information for complete box warning.

Complex sleep behaviors including sleep-walking, sleep-driving, and engaging in other activities while not fully awake may occur following use of Zolpidem Tartrate Sublingual Tablets. Some of these events may result in serious injuries, including death. Discontinue Zolpidem Tartrate Sublingual Tablets immediately if a patient experiences a complex sleep behavior (4, 5.1).

RECENT MAJOR CHANGES

Box Warning | 08/2019
Contraindications (4) | 08/2019
Warnings and Precautions, Complex Sleep Behaviors (5.1) | 08/2019
Warnings and Precautions, CNS Depressant Effects and Next-Day Impairment (5.2) | 08/2019

1 INDICATIONS AND USAGE

Zolpidem Tartrate is a GABAA agonist indicated for use as needed for the treatment of insomnia when a middle-of-the-night awakening is followed by difficulty returning to sleep (1)

Limitation of Use: Not indicated for the treatment of middle-of-the night awakening when the patient has fewer than 4 hours of bedtime remaining before the planned time of waking (1)

2 DOSAGE AND ADMINISTRATION

- Take only if 4 hours of bedtime remain before the planned time of waking (2.1, 5.1)
- Zolpidem Tartrate Sublingual Tablets should be placed under the tongue and allowed to disintegrate completely before swallowing. The tablet should not be swallowed whole. (2.1)
- The effect of Zolpidem Tartrate Sublingual Tablets may be slowed if taken with or immediately after a meal (2.1)
- Recommended dose is 1.75 mg for women and 3.5 mg for men, taken only once per night if needed (2.2)
- Lower doses of CNS depressants may be necessary when taken concomitantly with Zolpidem Tartrate Sublingual Tablets (2.3)
- Co-administration with CNS depressants: Recommended dose is 1.75 mg for men and women (2.3)
- Geriatric patients and patients with hepatic impairment: Recommended dose is 1.75 mg for men and women (2.4, 2.5)

3 DOSAGE FORMS AND STRENGTHS

1.75 mg and 3.5 mg sublingual tablets (3)

4 CONTRAINDICATIONS

- Patients who have experienced complex sleep behaviors after taking Zolpidem Tartrate Sublingual Tablets (4, 5.1)
- Known hypersensitivity to zolpidem (4)

5 WARNINGS AND PRECAUTIONS

- CNS depressant effects: Impairs alertness and motor coordination, including risk of morning impairment. Risk increases with dose and use with other CNS depressants and alcohol. Instruct patients on correct use (5.2)
- Evaluate for co-morbid diagnoses: Re-evaluate if insomnia persists after 7 to 10 days of use (5.2)
- Severe anaphylactic/anaphylactoid reactions: Angioedema and anaphylaxis have been reported. Do not re-challenge if such reactions occur (5.3)
- Abnormal Thinking and Behavioral Changes: Changes including decreased inhibition, bizarre behavior, agitation and depersonalization have been reported. Immediately evaluate any new onset behavioral changes (5.5)
- Depression: Worsening of depression or suicidal thinking may occur. Prescribe the least number of tablets feasible to avoid intentional overdose (5.6)
- Respiratory Depression: Consider this risk before prescribing in patients with compromised respiratory function (5.7)

6 ADVERSE REACTIONS

Most commonly observed adverse reactions (> 1% in adult patients) are headache, nausea, and fatigue. (6.1)

To report SUSPECTED ADVERSE REACTIONS, contact Lupin Pharmaceuticals, Inc. at 1-866-403-7592 or FDA at 1-800-FDA-1088 or http://www.fda.gov/medwatch

7 DRUG INTERACTIONS

- CNS depressants, including alcohol: Possible adverse additive CNS depressant effects (5.1, 7.1)
- Imipramine: Decreased alertness observed (7.1)
- Chlorpromazine: Impaired alertness and psychomotor performance observed (7.1)
- Rifampin: Combination use may decrease effects (7.2)
- Ketoconazole: Combination use may increase effects (7.2)

8 USE IN SPECIFIC POPULATIONS

- Pregnancy: Based on animal data, zolpidem may cause fetal harm. (8.1)
- Pediatric use: Safety and effectiveness of zolpidem not established. With bedtime dosing of zolpidem, hallucinations observed (incidence 7%) (8.4)

FULL PRESCRIBING INFORMATION

WARNING COMPLEX SLEEP BEHAVIORS

Complex sleep behaviors including sleep-walking, sleep-driving, and engaging in other activities while not fully awake may occur following use of Zolpidem Tartrate Sublingual Tablets. Some of these events may result in serious injuries, including death. Discontinue Zolpidem Tartrate Sublingual Tablets immediately if a patient experiences a complex sleep behavior [ see Contraindications (4) and Warnings and Precautions (5.1)].

1 INDICATIONS AND USAGE

Zolpidem Tartrate Sublingual Tablet is indicated for use as needed for the treatment of insomnia when a middle-of-the-night awakening is followed by difficulty returning to sleep.

Limitations of Use: Zolpidem Tartrate Sublingual Tablet is not indicated for the treatment of middle-of-the-night insomnia when the patient has fewer than 4 hours of bedtime remaining before the planned time of waking.

2 DOSAGE AND ADMINISTRATION

2.1 Important Administration Instructions

Zolpidem Tartrate Sublingual Tablet is to be taken in bed when a patient wakes in the middle of the night and has difficulty returning to sleep. Zolpidem Tartrate Sublingual Tablet should only be taken if the patient has at least 4 hours of bedtime remaining before the planned time of waking [see Warnings and Precautions (5.1)].

Zolpidem Tartrate Sublingual Tablet should be placed under the tongue and allowed to disintegrate completely before swallowing. The tablet should not be swallowed whole. For optimal effect, Zolpidem Tartrate Sublingual Tablet should not be administered with or immediately after a meal. The blister should be removed from the pouch just prior to dosing.

2.2 Basic Dosing Information

The recommended and maximum dose of Zolpidem Tartrate Sublingual Tablet is 1.75 mg for women and 3.5 mg for men, taken only once per night as needed if a middle-of-the-night awakening is followed by difficulty returning to sleep. The recommended doses for women and men are different because women clear zolpidem from the body at a lower rate than men [see Use in Specific Populations (8.6)] .

2.3 Use with CNS Depressants

The recommended Zolpidem Tartrate Sublingual Tablet dose for men and women who are taking concomitant CNS depressants is 1.75 mg. Dose adjustment of concomitant CNS depressants may be necessary when co-administered with Zolpidem Tartrate Sublingual Tablet because of potentially additive effects. The use of Zolpidem Tartrate Sublingual Tablet with other sedative-hypnotics (including other zolpidem products) at bedtime or the middle of the night is not recommended [see Warnings and Precautions (5.1)].

2.4 Use in Geriatric Patients

Geriatric patients may be especially sensitive to the effects of zolpidem. The recommended dose of Zolpidem Tartrate Sublingual Tablets in men and women over 65 years old is 1.75 mg, taken only once per night if needed [see Use in Specific Populations (8.5)].

2.5 Use in Patients with Hepatic Impairment

The recommended dose of Zolpidem Tartrate Sublingual Tablet in patients with hepatic impairment is 1.75 mg, taken only once per night if needed [see Clinical Pharmacology (12.3)].

3 DOSAGE FORMS AND STRENGTHS

Zolpidem Tartrate Sublingual Tablets are available as 1.75 mg and 3.5 mg tablets for sublingual administration.

Zolpidem Tartrate Sublingual Tablets 1.75 mg are white to off white, round, flat faced beveled edged tablets debossed with "N2"on one side and plain on the other side.

Zolpidem Tartrate Sublingual Tablets 3.5 mg are white to off white, round, flat faced beveled edged tablets debossed with "NP"on one side and plain on the other side.

4 CONTRAINDICATIONS

Zolpidem Tartrate Sublingual Tablets are contraindicated in patients who have experienced complex sleep behaviors after taking Zolpidem Tartrate Sublingual Tablets [see Warnings and Precautions (5.1)]

Zolpidem Tartrate Sublingual Tablets are contraindicated in patients with known hypersensitivity to zolpidem. Observed reactions with zolpidem include anaphylaxis and angioedema [see Warnings and Precautions (5.3)].

5 WARNINGS AND PRECAUTIONS

5.1 COMPLEX SLEEP BEHAVIORS

Complex sleep behaviors including sleep-walking, sleep-driving, and engaging in other activities while not fully awake may occur following the first or any subsequent use of zolpidem. Patients can be seriously injured or injure others during complex sleep behaviors. Such injuries may result in a fatal outcome. Other complex sleep behaviors (e.g., preparing and eating food, making phone calls, or having sex) have also been reported.

Patients usually do not remember these events. Post-marketing reports have shown that complex sleep behaviors may occur with zolpidem alone at recommended dosages, with or without the concomitant use of alcohol or other central nervous system (CNS) depressants [ see Drug Interactions (7.1)], .].

Discontinue Zolpidem Tartrate Sublingual Tablets immediately if a patient experiences a complex sleep behavior

5.2 CNS Depressant Effects and Next-Day Impairment

Zolpidem Tartrate Sublingual Tablets, like other sedative-hypnotic drugs, has central nervous system (CNS) depressant effects. Co-administration with other CNS depressants (e.g., benzodiazepines, opioids, tricyclic antidepressants, alcohol) increases the risk of CNS depression. Dosage adjustments of Zolpidem Tartrate Sublingual Tablets and of other concomitant CNS depressants may be necessary when Zolpidem Tartrate Sublingual Tablets are administered with such agents because of the potentially additive effects. The use of Zolpidem Tartrate Sublingual Tablets with other sedative-hypnotics (including other zolpidem products) at bedtime or the middle of the night is not recommended [ see Dosage and Administration (2.3)]

In a driving study, healthy subjects who received Zolpidem Tartrate Sublingual Tablets with fewer than four hours of bedtime remaining had evidence of impaired driving compared to subjects who received placebo [see Clinical Studies (14.2)]. The risk of next-day driving impairment (and psychomotor impairment) is increased if Zolpidem Tartrate Sublingual Tablets is taken with less than 4 hours of bedtime remaining, if higher than recommended dose is taken, if co-administered with other CNS depressants, or co-administered with other drugs that increase the blood levels of zolpidem.

Because Zolpidem Tartrate Sublingual Tablets can cause drowsiness and a decreased level of consciousness, patients, particularly the elderly, are at a higher risk of falls.

5.3 Need to Evaluate for Co-morbid Diagnoses

Because sleep disturbances may be the presenting manifestation of a physical and/or psychiatric disorder, symptomatic treatment of insomnia should be initiated only after a careful evaluation of the patient. The failure of insomnia to remit after 7 to 10 days of treatment may indicate the presence of a primary psychiatric and/or medical illness that should be evaluated. Worsening of insomnia or the emergence of new thinking or behavior abnormalities may be the consequence of an unrecognized psychiatric or physical disorder. Such findings have emerged during the course of treatment with sedative-hypnotic drugs, including zolpidem.

5.4 Severe Anaphylactic and Anaphylactoid Reactions

Cases of angioedema involving the tongue, glottis, or larynx have been reported in patients after taking the first or subsequent doses of zolpidem. Some patients have had additional symptoms such as dyspnea, throat closing, or nausea and vomiting that suggest anaphylaxis. Some patients have required medical therapy in the emergency department. If angioedema involves the throat, glottis or larynx, airway obstruction may occur and be fatal. Patients who develop angioedema or anaphylaxis after treatment with zolpidem should not be rechallenged with Zolpidem Tartrate Sublingual Tablets.

5.5 Abnormal Thinking and Behavioral Changes

Abnormal thinking and behavior changes have been reported in patients treated with sedative-hypnotics including zolpidem. Some of these changes included decreased inhibition (e.g., aggressiveness and extroversion that seemed out of character), bizarre behavior, agitation, and depersonalization. Visual and auditory hallucinations have also been reported.

In controlled trials of zolpidem tartrate 10 mg taken at bedtime, < 1% of adults with insomnia who received zolpidem reported hallucinations. In a clinical trial, 7% of pediatric patients treated with zolpidem tartrate 0.25 mg/kg taken at bedtime, reported hallucinations, versus 0% treated with placebo [see Use in Specific Populations (8.4)].

The emergence of any new behavioral sign or symptom of concern requires careful and immediate evaluation.

5.6 Use in Patients with Depression

In primarily depressed patients treated with sedative-hypnotics, worsening of depression, and suicidal thoughts and actions (including completed suicides), have been reported. Suicidal tendencies may be present in such patients and protective measures may be required. Intentional overdosage is more common in this group of patients; therefore, the lowest number of tablets that is feasible should be prescribed for the patient at any one time.

5.7 Respiratory Depression

Although studies with 10 mg zolpidem tartrate did not reveal respiratory depressant effects at hypnotic doses in healthy subjects or in patients with mild-to-moderate chronic obstructive pulmonary disease (COPD), a reduction in the Total Arousal Index, together with a reduction in lowest oxygen saturation and increase in the times of oxygen desaturation below 80% and 90%, was observed in patients with mild-to-moderate sleep apnea when treated with zolpidem compared to placebo. Since sedative-hypnotics have the capacity to depress respiratory drive, precautions should be taken if Zolpidem Tartrate Sublingual Tablets are prescribed to patients with compromised respiratory function. Post-marketing reports of respiratory insufficiency in patients receiving 10 mg of zolpidem tartrate, most of whom had pre-existing respiratory impairment, have been reported. The risks of respiratory depression should be considered prior to prescribing Zolpidem Tartrate Sublingual Tablets in patients with respiratory impairment including sleep apnea and myasthenia gravis.

5.8 Withdrawal Effects

There have been reports of withdrawal signs and symptoms following the rapid dose decrease or abrupt discontinuation of zolpidem. Monitor patients for tolerance, abuse, and dependence [see Drug Abuse and Dependence (9.2) and (9.3)].

Phenylketonurics

Phenylalanine is a component of aspartame. Each 3.5 mg and 1.75 mg Zolpidem Tartarate Sublingual Tablets contains 4.48 mg and 2.24 mg of phenylalanine.

6 ADVERSE REACTIONS

The following serious adverse reactions in zolpidem-treated patients are discussed in greater detail in other sections of the labeling:

- Complex Sleep Behaviors [ See Warnings and Precautions (5.1) ]
- CNS-Depressant Effects and Next-Day Impairment [ see Warnings and Precautions (5.2)]
- Serious Anaphylactic and Anaphylactoid Reactions [ see Warnings and Precautions (5.2) ]
- Abnormal Thinking and Behavioral Changes [ see Warnings and Precautions (5.5) ]
- Withdrawal Effects [ see Warnings and Precautions (5.8) ]

6.1 Clinical Trials Experience

The safety data described below are based on two double-blind placebo-controlled trials of Zolpidem Tartrate Sublingual Tablets in adult patients with insomnia characterized by difficulty returning to sleep after a middle-of-the-night awakening [see Clinical Studies (14.1)]. These two trials included 230 and 82 patients treated with 3.5 mg and 1.75 mg of Zolpidem Tartrate Sublingual Tablets, respectively. The first study was a 3-way crossover sleep-laboratory study in 82 patients (58 female and 24 male; median age 47 years; 51% Caucasian, 44% African-American) of 1.75 mg and 3.5 mg of Zolpidem Tartrate Sublingual Tablets compared to placebo (Study 1). The second study was a 4-week, parallel-group at-home study in 295 patients (201 female and 94 male; median age 43 years) of 3.5 mg of Zolpidem Tartrate Sublingual Tablets compared to placebo, used on an as needed basis after spontaneous middle-of-the-night awakenings (Study 2). In Study 2, patients took Zolpidem Tartrate Sublingual Tablets during the night on 62% of study nights.

Because clinical trials are conducted under widely varying conditions, adverse reaction rates observed in the clinical trials of a drug cannot be directly compared to rates in the clinical trials of another drug and may not reflect the rates observed in actual practice.

Table 1 shows the incidence of adverse reactions reported in Study 2 that occurred in 2% or more of Zolpidem Tartrate Sublingual Tablet-treated (3.5 mg) patients in which the incidence was greater than the incidence in placebo-treated patients. For women and other patients taking the 1.75 mg dose in Study 1, the incidence of adverse reactions was similar to the incidence seen with 3.5 mg of Zolpidem Tartrate Sublingual Tablets in Table 1.

The most commonly reported adverse reactions in all treatment groups were headache, nausea, and fatigue.

Table 1: Summary of Adverse Reactions (≥ 2%) in Outpatient, Double-Blind, Parallel-Group, Placebo-Controlled Study (Study 2)

MedDRA System Organ Class Preferred Term | 3.5 mg Zolpidem Tartrate Sublingual Tablets (n=150) | Placebo (n=145)
Gastrointestinal Disorders | 4% | 2%
Nausea | 1% | 1%
General Disorders and Administration Site Conditions | 3% | 0%
Fatigue | 1% | 0%
Nervous System Disorders | 5% | 3%
Headache | 3% | 1%

7 DRUG INTERACTIONS

7.1 CNS-active Drugs

Co-administration of zolpidem with other CNS depressants increases the risk of CNS depression [see Warnings and Precautions (5.2)]. Zolpidem tartrate was evaluated in healthy volunteers in single-dose interaction studies for several CNS drugs.

Imipramine

Imipramine in combination with zolpidem produced no pharmacokinetic interaction other than a 20% decrease in peak levels of imipramine, but there was an additive effect of decreased alertness. Similarly, chlorpromazine in combination with zolpidem produced no pharmacokinetic interaction, but there was an additive effect of decreased alertness and psychomotor performance.

Haloperidol

A study involving haloperidol and zolpidem revealed no effect of haloperidol on the pharmacokinetics or pharmacodynamics of zolpidem. The lack of a drug interaction following single-dose administration does not predict the absence of an effect following chronic administration.

Alcohol

An additive adverse effect on psychomotor performance between alcohol and oral zolpidem was demonstrated [see Warnings and Precautions (5.2)].

Sertraline

Concomitant administration of zolpidem and sertraline increases exposure to zolpidem and may increase the pharmacodynamic effect of zolpidem.

Fluoxetine

After multiple doses of zolpidem tartrate and fluoxetine, an increase in the zolpidem halflife (17%) was observed. There was no evidence of an additive effect in psychomotor performance [see Clinical Pharmacology (12.3)].

7.2 Drugs that Affect Drug Metabolism via Cytochrome P450

Some compounds known to inhibit CYP3A may increase exposure to zolpidem. The effect of other P450 enzymes on the exposure to zolpidem is not known.

Rifampin

Rifampin, a CYP3A4 inducer, significantly reduced the exposure to and the pharmacodynamic effects of zolpidem. Use of Rifampin in combination with zolpidem may decrease the efficacy of zolpidem.

Ketoconazole

Ketoconazole, a potent CYP3A4 inhibitor, increased the pharmacodynamic effects of zolpidem. Consideration should be given to using a lower dose of zolpidem when ketoconazole and zolpidem are given together.

8 USE IN SPECIFIC POPULATIONS

8.1 Pregnancy

Pregnancy Category C

There are no adequate and well-controlled studies of zolpidem in pregnant women. Studies in children to assess the effects of prenatal exposure to zolpidem have not been conducted; however, cases of severe neonatal respiratory depression have been reported when zolpidem was used at the end of pregnancy, especially when taken with other CNS-depressants. Children born to mothers taking sedative-hypnotic drugs may be at risk for withdrawal symptoms during the postnatal period. Neonatal flaccidity has also been reported in infants born to mothers who received sedative-hypnotic drugs during pregnancy. Zolpidem Tartrate Sublingual Tablets should be used during pregnancy only if the potential benefit outweighs the potential risk to the fetus.

Administration of zolpidem to pregnant rats and rabbits resulted in adverse effects on offspring at doses greater than the recommended human dose (RHD) of 3.5 mg/day (approximately 2.8 mg/day zolpidem base); however, teratogenicity was not observed.

When zolpidem was administered at oral doses of 4, 20, and 100 mg base/kg/day to pregnant rats during the period of organogenesis, dose-related decreases in fetal skull ossification were observed at all but the lowest dose, which is approximately 15 times the RHD on a mg/m^2 basis. In rabbits treated during organogenesis with zolpidem at oral doses of 1, 4, and 16 mg base/kg/day, increased embryo-fetal death and incomplete fetal skull ossification were seen at the highest dose tested. The no-effect dose for embryo-fetal toxicity in rabbits is approximately 30 times the RHD on a mg/m^2 basis.

Administration of zolpidem to rats at oral doses of 4, 20, and 100 mg base/kg/day during the latter part of pregnancy and throughout lactation produced decreased offspring growth and survival at all but the lowest dose, which is approximately 15 times the RHD on a mg/m2 basis.

8.3 Nursing Mothers

Zolpidem is excreted in human milk. The effect of zolpidem on the nursing infant is not known.

8.4 Pediatric Use

Zolpidem Tartrate Sublingual Tablets are not recommended for use in children. Safety and effectiveness of Zolpidem Tartrate Sublingual Tablets have not been established in pediatric patients below the age of 18.

In an 8-week study in pediatric patients (aged 6 to 17 years) with insomnia associated with ADHD, an oral solution of zolpidem tartrate dosed at 0.25 mg/kg at bedtime did not decrease sleep latency compared to placebo. Hallucinations were reported in 7% of the pediatric patients who received zolpidem; none of the pediatric patients who received placebo reported hallucinations.

8.5 Geriatric Use

Zolpidem Tartrate Sublingual Tablets dosage adjustment is necessary in geriatric patients. Sedating drugs may cause confusion and over-sedation in the elderly; elderly patients generally should be started on low doses of Zolpidem Tartrate Sublingual Tablets and observed closely [see Dosage and Administration (2.4), and Clinical Pharmacology (12.3)].

Clinical trial experience with other zolpidem formulations (5 mg to 10 mg oral zolpidem tartrate) given at bedtime:

A total of 154 patients in U.S.-controlled clinical trials and 897 patients in non-U.S. clinical trials who received oral zolpidem were ≥ 60 years of age. For a pool of U.S. patients receiving oral zolpidem tartrate at doses of ≤ 10 mg or placebo, there were three adverse reactions occurring at an incidence of at least 3% for zolpidem and for which the zolpidem incidence was at least twice the placebo incidence (see Table 2).

Falls in geriatric patients:

A total of 30/1,959 (2%) non-U.S. patients receiving other zolpidem formulations (5 mg to 10 mg oral zolpidem tartrate) reported falls, including 28/30 (93%) who were ≥ 70 years of age. Of these 28 patients, 23 (82%) were receiving zolpidem tartrate doses > 10 mg. A total of 24/1,959 (1%) non-U.S. patients receiving zolpidem reported confusion, including 18/24 (75%) who were ≥70 years of age. Of these 18 patients, 14 (78%) were receiving zolpidem tartrate doses >10 mg.

The dose of Zolpidem Tartrate Sublingual Tablets in elderly patients is 1.75 mg to minimize adverse effects related to impaired motor and/or cognitive performance and unusual sensitivity to sedative-hypnotic drugs.

Table 2: Adverse Reactions in Geriatric Patients in Pooled Trials of 5 mg to 10 mg of Oral Zolpidem Tartrate Given at Bedtime

Adverse Reaction | 5 to 10 mg Oral Zolpidem Tartrate | Placebo
Dizziness | 3% | 0%
Drowsiness | 5% | 2%
Diarrhea | 3% | 1%

8.6 Gender Difference in Pharmacokinetics

Women cleared zolpidem tartrate from the body after sublingual administration of a 3.5 mg dose of Zolpidem Tartrate Sublingual Tablets at a lower rate than men (2.7 mL/min/kg vs. 4.0 mL/min/kg). Cmax and AUC parameters of zolpidem were approximately 45% higher at the same dose in female subjects compared with male subjects. Given the higher blood levels of zolpidem tartrate in women compared to men at a given dose, the recommended dose of Zolpidem Tartrate Sublingual Tablets for women is 1.75 mg, and the recommended dose for adult men is 3.5 mg.

9 DRUG ABUSE AND DEPENDENCE

9.1 Controlled Substance

Zolpidem tartrate is classified as a Schedule IV controlled substance by federal regulation.

9.2 Abuse

Abuse and addiction are separate and distinct from physical dependence and tolerance. Abuse is characterized by misuse of the drug for non-medical purposes, often in combination with other psychoactive substances. Tolerance is a state of adaptation in which exposure to a drug induces changes that result in diminution of one or more of the drug effects over time. Tolerance may occur to both desired and undesired effects of drugs and may develop at different rates for different effects.

Addiction is a primary, chronic, neurobiological disease with genetic, psychosocial, and environmental factors influencing its development and manifestations. It is characterized by behaviors that include one or more of the following: impaired control over drug use, compulsive use, continued use despite harm, and craving. Drug addiction is a treatable disease, using a multidisciplinary approach, but relapse is common.

Studies of abuse potential in former drug abusers found that the effects of single doses of 40 mg of oral zolpidem tartrate were similar, but not identical, to diazepam 20 mg, while 10 mg of oral zolpidem tartrate was difficult to distinguish from placebo.

Because persons with a history of addiction to or abuse of drugs or alcohol are at increased risk for misuse, abuse and addiction of zolpidem, they should be monitored carefully when receiving Zolpidem Tartrate Sublingual Tablets.

9.3 Dependence

Physical dependence is a state of adaptation that is manifested by a specific withdrawal syndrome that can be produced by abrupt cessation, rapid dose reduction, decreasing blood level of the drug, and/or administration of an antagonist.

Sedative-hypnotics have produced withdrawal signs and symptoms following abrupt discontinuation. These reported symptoms range from mild dysphoria and insomnia to a withdrawal syndrome that may include abdominal and muscle cramps, vomiting, sweating, tremors, and convulsions. The following adverse events which are considered to meet the DSM-III-R criteria for uncomplicated sedative-hypnotic withdrawal were reported during U.S. clinical trials with other oral zolpidem formulations following placebo substitution occurring within 48 hours following the last zolpidem treatment: fatigue, nausea, flushing, lightheadedness, uncontrolled crying, emesis, stomach cramps, panic attack, nervousness, and abdominal discomfort. These reported adverse events occurred at an incidence of 1% or less. However, available data cannot provide a reliable estimate of the incidence, if any, of dependence during treatment at recommended doses. Post-marketing reports of abuse, dependence, and withdrawal resulting from use of oral zolpidem tartrate have been received.

10 OVERDOSAGE

10.1 Signs and Symptoms

In post-marketing experience of overdose with oral zolpidem tartrate alone, or in combination with CNS-depressant agents, impairment of consciousness ranging from somnolence to coma, cardiovascular and/or respiratory compromise, and fatal outcomes have been reported.

10.2 Recommended Treatment

General symptomatic and supportive measures should be used along with immediate gastric lavage where appropriate. Intravenous fluids should be administered as needed. Zolpidem's sedative-hypnotic effect was shown to be reduced by flumazenil and therefore flumazenil may be useful; however, flumazenil administration may contribute to the appearance of neurological symptoms (convulsions). As in all cases of drug overdose, respiration, pulse, blood pressure, and other appropriate signs should be monitored and general supportive measures employed. Hypotension and CNS depression should be treated by appropriate medical intervention. Sedating drugs should be withheld following zolpidem overdosage, even if excitation occurs. The value of dialysis in the treatment of overdosage has not been determined, although hemodialysis studies in patients with renal failure receiving therapeutic doses have demonstrated that zolpidem is not dialyzable.

As with management of all overdosage, the possibility of multiple drug ingestion should be considered. The healthcare provider may wish to consider contacting a poison control center for up-to-date information on the management of hypnotic drug overdosage.

11 DESCRIPTION

Zolpidem Tartrate Sublingual Tablets contains zolpidem tartrate, a non-benzodiazepine hypnotic of the imidazopyridine class. Zolpidem Tartrate Sublingual Tablets are available in 1.75 mg and 3.5 mg strength tablets for sublingual administration. Zolpidem Tartrate Sublingual Tablets are intended to be placed under the tongue where they will disintegrate.

Zolpidem Tartrate Sublingual Tablets contain a bicarbonate-carbonate buffer.

Chemically, zolpidem tartrate is N,N-6-trimethyl-2- p-tolylimidazo[1,2- α]pyridine-3-acetamide L-(+)-tartrate (2:1).

Zolpidem tartrate is a white to almost white crystalline powder that is sparingly soluble in water, alcohol, and propylene glycol. It has a molecular weight of 764.88.

Each Zolpidem Tartrate Sublingual Tablet includes the following inactive ingredients: Crospovidone, Povidone, Mannitol, Polyvinylacetate, colloidal silicon dioxide, sodium carbonate anhydrous, sodium bicarbonate, natural and artificial spearmint flavor, aspartame, and magnesium stearate.

12 CLINICAL PHARMACOLOGY

12.1 Mechanism of Action

Zolpidem, the active moiety of zolpidem tartrate, is a hypnotic agent with a chemical structure unrelated to benzodiazepines, barbiturates, or other drugs with known hypnotic properties. It interacts with a GABA-BZ complex and shares some of the pharmacological properties of the benzodiazepines. In contrast to the benzodiazepines, which nonselectively bind to and activate all BZ receptor subtypes, zolpidem in vitro binds the BZ1 receptor preferentially with a high affinity ratio of the alpha1/alpha5 subunits. This selective binding of zolpidem on the BZ1 receptor is not absolute, but it may explain the relative absence of myorelaxant and anticonvulsant effects in animal studies as well as the preservation of deep sleep (stages 3 and 4) in human studies of zolpidem at hypnotic doses.

12.3 Pharmacokinetics

Absorption

Zolpidem Tartrate Sublingual Tablets disintegrates in the sublingual cavity after administration. On average, Zolpidem Tartrate Sublingual Tablets are rapidly absorbed in both genders, with a mean Tmax across studies of about 35 minutes to about 75 minutes.

In healthy normal volunteers (age 21 to 45 years) dosed with 3.5 mg Zolpidem Tartrate Sublingual Tablets, the average Cmax and AUC were 77 ng/mL and 296 ng·h/mL, respectively in women. The average Cmax and AUC were 53 ng/mL and 198 ng·h/mL, respectively in men. In women, the average Cmax and AUC of the 1.75 mg Zolpidem Tartrate Sublingual Tablets dose were 37 ng/mL and 151 ng·h/mL, respectively.

Food decreased the overall Cmax and AUC of Zolpidem Tartrate Sublingual Tablets 3.5 mg by 42% and 19%, respectively, and increased the time to peak exposure (Tmax) to nearly 3 hours. For optimal effect, Zolpidem Tartrate Sublingual Tablets should not be administered with or immediately after a meal.

Distribution

Based on data obtained with oral zolpidem, the total protein binding was found to be 93% ± 0.1% and remained constant independent of concentration between 40 ng/mL and 790 ng/mL.

Metabolism

Based on data obtained with oral zolpidem, zolpidem tartrate is converted to inactive metabolites that are eliminated primarily by renal excretion.

Elimination

The elimination half-life of a single dose of a 3.5 mg Zolpidem Tartrate Sublingual Tablet is approximately 2.5 hours (range 1.4 to 3.6 hours).

Special Populations

Elderly: The recommended dose for Zolpidem Tartrate Sublingual Tablets is 1.75 mg. A pharmacokinetic study of 1.75 mg and 3.5 mg doses of Zolpidem Tartrate Sublingual Tablets showed that the plasma Cmax and AUC0-4hr in elderly subjects following the 3.5 mg dose was higher by 34% and 30%, respectively, than the non-elderly subjects. The Cmax and AUC of 1.75 mg in elderly subjects were consistently lower than those observed for the 3.5 mg dose in non-elderly subjects but consistently higher than the 1.75 mg dose in non-elderly subjects. The elimination half-life remained unchanged.

Hepatic Impairment: The pharmacokinetics of oral zolpidem tartrate in eight patients with chronic hepatic insufficiency were compared to results in subjects with normal hepatic function. Following a single 20 mg oral zolpidem tartrate dose, mean Cmax and AUC were found to be two times (250 ng/mL vs. 499 ng/mL) and five times (788 ng·hr/mL vs. 4203 ng·hr/mL) higher, respectively, in hepatically compromised patients compared to subjects with normal hepatic function. Tmax did not change. The mean half-life in cirrhotic patients of 9.9 hr (range: 4.1 to 25.8 hr) was greater than that observed in subjects with normal hepatic function of 2.2 hr (range: 1.6 to 2.4 hr). Dosing should be modified accordingly in patients with hepatic insufficiency [see Dosage and

Administration (2.5)].

Renal Impairment: The pharmacokinetics of zolpidem tartrate were studied in 11 patients with end-stage renal failure (mean ClCr = 6.5 ± 1.5 mL/min) undergoing hemodialysis three times a week, who were dosed with zolpidem tartrate 10 mg orally each day for 14 or 21 days. No statistically significant differences were observed for Cmax, Tmax, half-life, and AUC between the first and last day of drug administration when baseline concentration adjustments were made. Zolpidem was not hemodialyzable. No accumulation of unchanged drug appeared after 14 or 21 days. Zolpidem pharmacokinetics were not significantly different in renally-impaired patients. No dosage adjustment is necessary in patients with renal impairment.

Drug Interactions

CNS-depressants

Co-administration of zolpidem with other CNS depressants increases the risk of CNS depression [see Warnings and Precautions (5.1)]. Zolpidem tartrate was evaluated in healthy volunteers in single-dose interaction studies for several CNS drugs. Imipramine in combination with zolpidem produced no pharmacokinetic interaction other than a 20% decrease in peak levels of imipramine, but there was an additive effect of decreased alertness. Similarly, chlorpromazine in combination with zolpidem produced no pharmacokinetic interaction, but there was an additive effect of decreased alertness and psychomotor performance.

A study involving haloperidol and zolpidem revealed no effect of haloperidol on the pharmacokinetics or pharmacodynamics of zolpidem. The lack of a drug interaction following single-dose administration does not predict the absence of an effect following chronic administration.

An additive adverse effect on psychomotor performance between alcohol and oral zolpidem was demonstrated [see Warnings and Precautions (5.1)].

Following five consecutive nightly doses at bedtime of oral zolpidem tartrate 10 mg in the presence of sertraline 50 mg (17 consecutive daily doses, at 7:00 am, in healthy female volunteers), zolpidem Cmax was significantly higher (43%) and Tmax was significantly decreased (-53%). Pharmacokinetics of sertraline and N-desmethylsertraline were unaffected by zolpidem.

A single-dose interaction study with zolpidem tartrate 10 mg and fluoxetine 20 mg at steady-state levels in male volunteers did not demonstrate any clinically significant pharmacokinetic or pharmacodynamic interactions. When multiple doses of zolpidem and fluoxetine were given at steady state and the concentrations evaluated in healthy females, an increase in the zolpidem half-life (17%) was observed. There was no evidence of an additive effect in psychomotor performance.

Drugs that Affect Drug Metabolism via Cytochrome P450

Some compounds known to inhibit CYP3A may increase exposure to zolpidem. The effect of inhibitors of other P450 enzymes on the pharmacokinetics of zolpidem is unknown.

A single-dose interaction study with zolpidem tartrate 10 mg and itraconazole 200 mg at steady-state levels in male volunteers resulted in a 34% increase in AUC0-∞ of zolpidem tartrate. There were no pharmacodynamic effects of zolpidem detected on subjective drowsiness, postural sway, or psychomotor performance.

A single-dose interaction study with zolpidem tartrate 10 mg and rifampin 600 mg at steady-state levels in female subjects showed significant reductions of the AUC (-73%), Cmax (-58%), and T1/2 (-36 %) of zolpidem together with significant reductions in the pharmacodynamic effects of zolpidem tartrate. Rifampin, a CYP3A4 inducer, significantly reduced the exposure to and the pharmacodynamic effects of zolpidem.

A single-dose interaction study with zolpidem tartrate 5 mg and ketoconazole, a potent CYP3A4 inhibitor, given as 200 mg twice daily for 2 days increased Cmax of zolpidem (30%) and the total AUC of zolpidem (70%) compared to zolpidem alone and prolonged the elimination half-life (30 %) along with an increase in the pharmacodynamic effects of zolpidem. Consideration should be given to using a lower dose of zolpidem when ketoconazole and zolpidem are given together.

Other Drugs with No Interactions with Zolpidem

A study involving cimetidine/zolpidem tartrate and ranitidine/zolpidem tartrate combinations revealed no effect of either drug on the pharmacokinetics or pharmacodynamics of zolpidem.

Zolpidem tartrate had no effect on digoxin pharmacokinetics and did not affect prothrombin time when given with warfarin in healthy subjects.

13 NONCLINICAL TOXICOLOGY

13.3 Carcinogenesis, Mutagenesis, Impairment of Fertility

Carcinogenesis: Zolpidem was administered in the diet to rats and mice for 2 years at doses of 4, 18, and 80 mg base/kg/day. In mice, these doses are approximately 7, 30, and 140 times, respectively, the recommended human dose (RHD) of 3.5 mg/day (approximately 2.8 mg zolpidem base) on a mg/m^2 basis. In rats, these doses are approximately 15, 60, and 280 times, respectively, the RHD on a mg/m^2 basis. No evidence of carcinogenic potential was observed in mice. In rats, renal tumors (lipoma, liposarcoma) were seen at the mid- and high doses.

Mutagenesis: Zolpidem was negative in in vitro (bacterial reverse mutation, mouse lymphoma, and chromosomal aberration) and in vivo (mouse micronucleus) genetic toxicology assays.

Impairment of fertility: Oral administration of zolpidem (doses of 4, 20, and 100 mg base/kg/day) to rats prior to and during mating, and continuing in females through postpartum day 25, resulted in irregular estrus cycles and prolonged precoital intervals at the highest dose tested. The no-effect dose for these findings is approximately 70 times the RHD on a mg/m^2 basis. There was no impairment of fertility at any dose tested.

14 CLINICAL STUDIES

14.1 Middle-of-the-Night Awakening Trials

Zolpidem Tartrate Sublingual Tablets were evaluated in two randomized, double-blind, placebo-controlled studies (Studies 1 and 2) in patients with insomnia characterized by difficulty returning to sleep after a middle-of-the-night (MOTN) awakening. In these studies, patients met the diagnosis for primary insomnia as defined by the Diagnostic and Statistical Manual of Mental Disorders (DSM-IV-TR) and had at least three prolonged MOTN awakenings per week that were at least 30 minutes in duration.

Sleep Laboratory Study (Scheduled Dosing)

Adult patients aged 19 to 64 years (N=82; 58 female, 24 male) with a history of difficulty returning to sleep after middle-of-the-night awakenings were evaluated in a double-blind, placebo-controlled, 3-period cross-over sleep laboratory study (Study 1). The primary outcome measure was latency to persistent sleep (LPS).

Doses of 3.5 mg and 1.75 mg of Zolpidem Tartrate Sublingual Tablets significantly decreased both objective (by polysomnography) and subjective (patient-estimated) sleep latency after a scheduled middle-of-the-night awakening as compared to placebo. The effect on sleep latency was similar for females receiving 1.75 mg of Zolpidem Tartrate Sublingual Tablets and males receiving 3.5 mg of Zolpidem Tartrate Sublingual Tablets.

Outpatient Study (As-needed Dosing)

Adult patients aged 18 to 64 years (N=295; 201 women, 94 men) with difficulty returning to sleep after middle-of-the-night awakenings were evaluated in a double-blind, placebo-controlled 4-week outpatient study of Zolpidem Tartrate Sublingual Tablets. Patients took study drug (3.5 mg of Zolpidem Tartrate Sublingual Tablets or placebo) on an as needed (prn) basis, when they had difficulty returning to sleep after waking in the middle of the night, provided they had at least 4 hours time remaining in bed. Subjective (patient-estimated) time to fall back to sleep after middleof-the-night awakening was significantly shorter for Zolpidem Tartrate Sublingual Tablets 3.5 mg compared to placebo.

14.2 Special Safety Studies

Driving Study

A randomized, double-blind, placebo-controlled, active-control, single-center, four-period, crossover study in 40 healthy subjects was conducted to evaluate the effects of middle-of-the-night administration of Zolpidem Tartrate Sublingual Tablets on next-morning driving performance. The four randomized treatments included Zolpidem Tartrate Sublingual Tablets 3.5 mg four hours before driving, Zolpidem Tartrate Sublingual Tablets 3.5 mg three hours before driving, placebo, and a positive control (an unapproved sedative-hypnotic) given nine hours before driving.

The primary outcome measure was the change in the standard deviation of lateral position (SDLP), a measure of driving impairment. The results were analyzed using a symmetry analysis, which determined the proportion of subjects whose change from their own SDLP in the placebo condition was statistically significantly above a threshold thought to reflect clinically meaningful driving impairment.

When driving began 3 hours after taking Zolpidem Tartrate Sublingual Tablets, testing had to be terminated for one subject (a 23-year old woman) due to somnolence. Overall, the symmetry analysis showed a statistically significant impairing effect at 3 hours. When driving began 4 hours after taking Zolpidem Tartrate Sublingual Tablets, statistically significant impairment was not found, but numerically Zolpidem Tartrate Sublingual Tablets was worse than placebo. Zolpidem blood levels were not measured in the driving study, and the study was not designed to correlate specific blood level with degree of impairment. However, the estimated blood level of zolpidem in patients whose SDLP worsened according to the symmetry analysis is considered to present a risk for driving impairment. In some women, the 3.5 mg dose of Zolpidem Tartrate Sublingual Tablets results in zolpidem blood levels that remain at or sometimes considerably above this level 4 or more hours after dosing. Therefore, the recommended dose for women is 1.75 mg. A small negative effect on SDLP may remain in some patients 4 hours after the 1.75 mg dose in women, and after the 3.5 mg dose in men, such that a potential negative effect on driving cannot be completely excluded.

Rebound effects

In studies performed with other zolpidem formulations (5 mg to 10 mg oral zolpidem tartrate) given at bedtime, there was no objective (polysomnographic) evidence of rebound insomnia at recommended doses seen in studies evaluating sleep on the nights following discontinuation. There was subjective evidence of impaired sleep in the elderly on the first post-treatment night at doses above the recommended elderly dose of 5 mg oral zolpidem tartrate.

Memory impairment in controlled studies

Controlled studies in adults utilizing objective measures of memory yielded no consistent evidence of next-day memory impairment following the administration at bedtime of 5 mg to 10 mg oral zolpidem tartrate. However, in one study involving zolpidem tartrate doses of 10 mg and 20 mg, there was a significant decrease in next-morning recall of information presented to subjects during peak drug effect (90 minutes post-dose), i.e., these subjects experienced anterograde amnesia. There was also subjective evidence from adverse event data for anterograde amnesia occurring in association with the administration of oral zolpidem tartrate, predominantly at doses above 10 mg.

16 HOW SUPPLIED/STORAGE AND HANDLING

Each Zolpidem Tartrate Sublingual Tablet is individually packaged in a blister inside a unit-dose pouch.

Zolpidem Tartrate Sublingual Tablets 1.75 mg are white to off white, round, flat faced beveled edged debossed with "N2" on one side and plain on the other side and supplied as:

NDC 43386-762-30: Carton of 30 unit-dose pouches

Zolpidem Tartrate Sublingual Tablets 3.5 mg are white to off white, round, flat faced beveled edged debossed with "NP" on one side and plain on the other side and supplied as:

NDC 43386-761-30: Carton of 30 unit-dose pouches

Storage and Handling

Store between 20°C to 25°C (68°F to 77°F), [see USP Controlled Room Temperature]. Protect from moisture.

The patient should be instructed not to remove the blister from the unit-dose pouch until the patient is ready to consume the sublingual tablet inside.

Do not use if blister seal is broken or missing.

17 PATIENT COUNSELING INFORMATION

See FDA-approved patient labeling (Medication Guide).

Inform patients and their families about the benefits and risks of treatment with Zolpidem Tartrate Sublingual Tablets. Inform patients of the availability of a Medication Guide and instruct them to read the Medication Guide prior to initiating treatment with Zolpidem Tartrate Sublingual Tablets and with each prescription refill. Review the Zolpidem Tartrate Sublingual Tablets Medication Guide with every patient prior to initiation of treatment. Instruct patients or caregivers that Zolpidem Tartrate Sublingual Tablets should be taken only as prescribed.

Complex Sleep Behaviors

Instruct patients and their families that Zolpidem Tartrate Sublingual Tablets may cause complex sleep behaviors, including sleep-walking, sleep-driving, preparing and eating food, making phone calls, or having sex while not being fully awake. Serious injuries and death have occurred during complex sleep behavior episodes. Tell patients to discontinue Zolpidem Tartrate Sublingual Tablets and notify their healthcare provider immediately if they develop any of these symptoms [see Boxed Warning, Warnings and Precautions (5.1)]

CNS depressant Effects and Next-Day Impairment

Tell patients that Zolpidem Tartrate Sublingual Tablets has the potential to cause next-day impairment, and that this risk is increased if dosing instructions are not carefully followed. Tell patients to wait for at least 4 hours after dosing and until they feel fully awake before driving or engaging in other activities requiring full mental alertness.

Severe Anaphylactic and Anaphylactoid Reactions

Inform patients that severe anaphylactic and anaphylactoid reactions have occurred with zolpidem. Describe the signs/symptoms of these reactions and advise patients to seek medical attention immediately if any of them occur.

Suicide

Tell patients to immediately report any suicidal thoughts.

Administration Instructions

For detailed instructions on how to use Zolpidem Tartrate Sublingual Tablets, tell patients to refer to the Patient Instructions for Use.

Tell patients that Zolpidem Tartrate Sublingual Tablets are to be taken only once per night if needed if they wake in the middle of the night and have difficulty returning to sleep. Tell patients that Zolpidem Tartrate Sublingual Tablets should only be taken if they have 4 hours of bedtime remaining before the planned time of waking.

Instruct the patient to place the tablet under the tongue, allowing it to disintegrate completely before swallowing. Tell the patient that Zolpidem Tartrate Sublingual Tablets should not be swallowed whole.

Tell patients that the effect of Zolpidem Tartrate Sublingual Tablets may be slowed if taken with or immediately after a meal.

Instruct patients to remove the blister from the unit-dose pouch just prior to dosing.

Advise patients NOT to take Zolpidem Tartrate Sublingual Tablets if they drank alcohol that day or before bed.

Manufactured by:

Novel Laboratories. Inc.

Somerset, NJ 08873

Manufactured for:

Lupin Pharmaceuticals, Inc.

Baltimore, MD 21202

Rev. 12/2019

PI7610000205

SAP code: 263479

MEDICATION GUIDE

Zolpidem Tartrate ((zol' pi dem tar' trate)) Sublingual Tablet CIV

Phenylketonurics

Phenylalanine is a component of aspartame. Each 3.5 mg and 1.75 mg Zolpidem Tartarate Sublingual Tablets contains 4.48 mg and 2.24 mg of phenylalanine.

Read the Medication Guide that comes with Zolpidem Tartrate Sublingual Tablets before you start taking it and each time you get a refill. There may be new information. This Medication Guide does not take the place of talking to your doctor about your medical condition or treatment.

What is the most important information I should know about Zolpidem Tartrate Sublingual Tablet?

Follow the Instructions for Use at the end of this Medication Guide when you take Zolpidem Tartrate Sublingual Tablet. If you do not follow the Instructions for Use, you might be drowsy in the morning without knowing it.

- Only take one Tablet a night, if needed.
- Only take Zolpidem Tartrate Sublingual Tablet if you have at least 4 hours of bedtime left.

Zolpidem Tartrate Sublingual Tablet may cause serious side effects, including:

- Complex sleep behaviors that have caused serious injury and death . After taking Zolpidem Tartrate Sublingual Tablets, you may get up out of bed while not being fully awake and do an activity that you do not know you are doing (complex sleep behaviors). The next morning, you may not remember that you did anything during the night. These activities may occur with Zolpidem Tartrate Sublingual Tablets whether or not you drink alcohol or take other medicines that make you sleepy

Reported activities include:

- driving a car ("sleep-driving")
- making and eating food
- talking on the phone
- having sex
- sleep-walking

Stop taking Zolpidem Tartrate Sublingual Tablet and call your healthcare provider right away if you find out that you have done any of the above activities after taking Zolpidem Tartrate Sublingual Tablet.

Important:

1. Take Zolpidem Tartrate Sublingual Tablet exactly as prescribed
2. Do not take Zolpidem Tartrate Sublingual Tablet if you:
  - have ever experienced a complex sleep behavior (such as driving a car, making and eating food, talking on the phone or having sex while not fully awake) after taking Zolpidem Tartrate Sublingual Tablet
  - drank alcohol that day or before bed.
  - took another medicine to help you sleep.
  - do not have at least 4 hours of bedtime remaining.

What is Zolpidem Tartrate Sublingual Tablet?

Zolpidem Tartrate Sublingual Tablet is a sedative-hypnotic (sleep) medicine. Zolpidem Tartrate Sublingual Tablet is used in adults for the treatment of a sleep problem called insomnia. Many people have difficulty returning to sleep after awakening in the middle of the night. Zolpidem Tartrate Sublingual Tablet is designed to specifically treat this problem.

It is not known if Zolpidem Tartrate Sublingual Tablet is safe and effective in children.

Zolpidem Tartrate Sublingual Tablet is a federally controlled substance (CIV) because it can be abused or lead to dependence. Keep Zolpidem Tartrate Sublingual Tablet in a safe place to prevent misuse and abuse. Selling or giving away Zolpidem Tartrate Sublingual Tablet may harm others, and is against the law. Tell your doctor if you have ever abused or have been dependent on alcohol, prescription medicines, or street drugs.

Who should not take Zolpidem Tartrate Sublingual Tablet?

- Do not take Zolpidem Tartrate Sublingual Tablets if you have ever had a complex sleep behavior happen after taking Zolpidem Tartrate Sublingual Tablets.
- Do not take Zolpidem Tartrate Sublingual Tablet if you are allergic to zolpidem or any other ingredients in Zolpidem Tartrate Sublingual Tablet. See the end of this Medication Guide for a complete list of ingredients in Zolpidem Tartrate Sublingual Tablet.
- Do not take Zolpidem Tartrate Sublingual Tablet if you have had an allergic reaction to drugs containing zolpidem, such as Ambien, Ambien CR, Edluar, or Zolpimist.

Symptoms of a serious allergic reaction to Zolpidem Tartrate Sublingual Tablet can include:

- swelling of your face, lips, and throat that may cause difficulty breathing or swallowing
- nausea and vomiting

Zolpidem Tartrate Sublingual Tablet may not be right for you. Before starting Zolpidem Tartrate Sublingual Tablet, tell your doctor about all of your health conditions, including if you:

- have a history of depression, mental illness, or suicidal thoughts
- have a history of drug or alcohol abuse or addiction
- have kidney or liver disease
- have a lung disease or breathing problems
- are pregnant, planning to become pregnant, or breastfeeding

Tell your doctor about all of the medicines you take, including prescription and nonprescription medicines, vitamins, and herbal supplements. Medicines can interact with each other, sometimes causing serious side effects. Your doctor will tell you if you can take Zolpidem Tartrate Sublingual Tablet with your other medicines.

Know the medicines you take. Keep a list of your medicines with you to show your doctor and pharmacist each time you get a new medicine.

How should I take Zolpidem Tartrate Sublingual Tablet?

- See "What is the most important information I should know about Zolpidem Tartrate Sublingual Tablet "
- Read the " Instructions for Use" at the end of this Medication Guide for detailed instructions on how to take Zolpidem Tartrate Sublingual Tablet.
- Take Zolpidem Tartrate Sublingual Tablet exactly as prescribed. Only take one Zolpidem Tartrate Sublingual Tablet per night if needed.
- Do not take Zolpidem Tartrate Sublingual Tablet if you drank alcohol that evening or before bed.
- While in bed, place the tablet under your tongue and allow it to break apart completely. Do not swallow it whole.
- You should not take Zolpidem Tartrate Sublingual Tablet with or right after a meal. Zolpidem Tartrate Sublingual Tablet may help you fall asleep faster when you take it on an empty stomach.
- Call your health care provider if your insomnia worsens or is not better within 7 to 10 days. This may mean that there is another condition causing your sleep problem.
- If you take too much Zolpidem Tartrate Sublingual Tablet or overdose get emergency treatment.

What are the possible side effects of Zolpidem Tartrate Sublingual Tablet?

Zolpidem Tartrate Sublingual Tablet may cause serious side effects, including:

- getting out of bed while not being fully awake and doing an activity that you do not know you are doing. (See "What is the most important information I should know about Zolpidem Tartrate Sublingual Tablet?")
- abnormal thoughts and behavior. Symptoms include more outgoing or aggressive behavior than normal, confusion, agitation, hallucinations, worsening of depression, and suicidal thoughts or actions.
- memory loss
- anxiety
- severe allergic reactions. Symptoms include swelling of the tongue or throat, trouble breathing, and nausea and vomiting. Get emergency medical help if you get these symptoms after taking Zolpidem Tartrate Sublingual Tablet.

Call your health care provider right away if you have any of the above side effects or any other side effects that worry you while using Zolpidem Tartrate Sublingual Tablet.

The most common side effects of Zolpidem Tartrate Sublingual Tablet are:

- Headache
- Nausea
- Fatigue

Even if you follow the Instructions for Use, you may still feel drowsy in the morning after taking Zolpidem Tartrate Sublingual Tablet. Do not drive or do other dangerous activities after taking Zolpidem Tartrate Sublingual Tablet until you are fully awake.

These are not all the side effects of Zolpidem Tartrate Sublingual Tablet. Ask your health care provider or pharmacist for more information.

You may report side effects to FDA at 1-800-FDA-1088.

How should I store Zolpidem Tartrate Sublingual Tablet?

- Store Zolpidem Tartrate Sublingual Tablet at room temperature, 68° to 77°F (20° to 25°C). Protect from moisture.
- Only remove the blister from the pouch when you are ready to use Zolpidem Tartrate Sublingual Tablet.

Keep Zolpidem Tartrate Sublingual Tablet and all medicines out of reach of children.

General Information about Zolpidem Tartrate Sublingual Tablet

Medicines are sometimes prescribed for purposes other than those listed in a Medication Guide. Do not use Zolpidem Tartrate Sublingual Tablet for a condition for which it was not prescribed. Do not give Zolpidem Tartrate Sublingual Tablet to other people, even if you think they have the same symptoms that you have. It may harm them and it is against the law.

This Medication Guide summarizes the most important information about Zolpidem Tartrate Sublingual Tablet . If you would like more information, talk with your doctor. You can ask your doctor or pharmacist for information about Zolpidem Tartrate Sublingual Tablet that is written for healthcare professionals.

What are the ingredients in Zolpidem Tartrate Sublingual Tablet?

Active Ingredient: Zolpidem tartrate

Inactive Ingredients: Each Zolpidem Tartrate Sublingual Tablet includes the following inactive ingredients: Crospovidone, Povidone, Mannitol, Polyvinylacetate, colloidal silicon dioxide, sodium carbonate anhydrous, sodium bicarbonate, natural and artificial spearmint flavor, aspartame, and magnesium stearate.

Rx only

This Medication Guide has been approved by the U.S. Food and Drug Administration.

Manufactured by:

Novel Laboratories, Inc.

Somerset, NJ 08873

Manufactured for:

Lupin Pharmaceuticals, Inc. Baltimore, MD 21202

Rev. 12/2019

Instructions for Use

Zolpidem Tartrate ((zol' pi dem tar' trate)) Sublingual Tablet CIV

Read these Instructions for Use before you start taking Zolpidem Tartrate Sublingual Tablet and each time you get a refill. There may be new information. This information does not take the place of talking to your healthcare provider about your medical condition or your treatment.

What is the most important Information I should know about Zolpidem Tartrate Sublingual Tablet?

Follow these Instructions for Use when you take Zolpidem Tartrate Sublingual Tablet. If you do not follow these instructions, you might be drowsy in the morning without knowing it.

- Only take 1 tablet a night if needed
- Only take Zolpidem Tartrate Sublingual Tablet if you have at least 4 hours of bedtime left

Using Zolpidem Tartrate Sublingual Tablet the wrong way can make you drowsy in the morning.

Before you go to bed:

- Place only 1 Zolpidem Tartrate Sublingual Tablet pouch by your bed, and have a clock or watch nearby (see Figure A).

- Store all other unopened Zolpidem Tartrate Sublingual Tablet pouches with your other medicines away from your bedside.
- Only remove the blister from the Zolpidem Tartrate Sublingual Tablet pouch when you are ready to use it.
- You can either use the Zolpidem Tartrate Sublingual Tablet Dosing Time Chart (see Figure B) or the Dosing Time Tool (see Figure C) that comes with Zolpidem Tartrate Sublingual Tablet to find the latest time during the night you can take Zolpidem Tartrate Sublingual Tablet.

Zolpidem Tartrate Sublingual Tablet Dosing Time Chart (see Figure B):

- You can take Zolpidem Tartrate Sublingual Tablet if you have at least 4 hours of bedtime left before you must be awake.
- Find the earliest time you have to be up and awake in the column on the left.
- Find the latest time you can take Zolpidem Tartrate Sublingual Tablet on the same line in the column on the right.

Zolpidem Tartrate Sublingual Tablet Dosing Time Tool (see Figure C):

- Turn the Zolpidem Tartrate Sublingual Tablet Dosing Time Tool wheel to show the earliest time that you must be awake under the green arrow.
- Take Zolpidem Tartrate Sublingual Tablet before the time under the black arrow.

During the night when you take Zolpidem Tartrate Sublingual Tablet:

Step 1. Check the current time and use the Zolpidem Tartrate Sublingual Tablet Dosing Time Chart or the Zolpidem Tartrate Sublingual Tablet Dosing Time Tool to decide if you should take Zolpidem Tartrate Sublingual Tablet.

- Only take Zolpidem Tartrate Sublingual Tablet if you have at least 4 hours of bedtime left before you have to be awake (see Figure B).

Step 2. Remove the blister from the Zolpidem Tartrate Sublingual Tablet pouch you placed by your bed (see Figure D).

Step 3. Cut blister with scissors at dotted line and take the Zolpidem Tartrate Sublingual Tablet out. (see Figure E).

Step 4. Leave the empty Zolpidem Tartrate Sublingual Tablet pouch where you can see it. The empty pouch will help remind you that you already took your Zolpidem Tartrate Sublingual Tablet dose (see Figure F).

Step 5. While in bed, place the Zolpidem Tartrate Sublingual Tablet under your tongue and allow it to break apart completely, then swallow. Do not swallow it whole. (see Figure G)

Step 6. Throw the empty Zolpidem Tartrate Sublingual Tablet pouch away in the morning.

When you wake up in the morning, be sure that at least 4 hours have passed since you have taken Zolpidem Tartrate Sublingual Tablet and you feel fully awake before driving. Do not do dangerous activities until you know how Zolpidem Tartrate Sublingual Tablet affects you.

This Medication Guide and Instructions for Use have been approved by the U.S. Food and Drug Administration.

Manufactured by:

Novel Laboratories, Inc.

400 Campus Drive,

Somerset, NJ 08873

Manufactured for:

Lupin Pharmaceuticals, Inc.

Baltimore, MD 21202

Rev. 12/2019

PI7610000205

SAP code: 263479

PACKAGE LABEL.PRINCIPAL DISPLAY PANEL

1.75 mg - Carton

3.5 mg – Carton

1.75 mg – Pouch

3.5 mg – Pouch

1.75 mg – Blister

3.5 mg – Blister